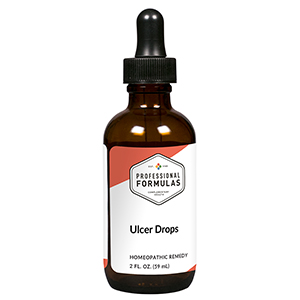 DRUG LABEL: Ulcer Drops
NDC: 63083-2094 | Form: LIQUID
Manufacturer: Professional Complementary Health Formulas
Category: homeopathic | Type: HUMAN OTC DRUG LABEL
Date: 20190815

ACTIVE INGREDIENTS: GLYCYRRHIZA GLABRA 2 [hp_X]/59 mL; SODIUM PHOSPHATE, DIBASIC, HEPTAHYDRATE 2 [hp_X]/59 mL; STARCH, RICE 2 [hp_X]/59 mL; PANICUM MILIACEUM WHOLE 2 [hp_X]/59 mL; PLANTAGO LANCEOLATA LEAF 2 [hp_X]/59 mL; FU LING 2 [hp_X]/59 mL; DAIKON 2 [hp_X]/59 mL; BLACK MUSTARD SEED 2 [hp_X]/59 mL; ELYMUS REPENS ROOT 2 [hp_X]/59 mL; GINGER 2 [hp_X]/59 mL; GOLDENSEAL 5 [hp_X]/59 mL; ACTIVATED CHARCOAL 6 [hp_X]/59 mL; COMFREY ROOT 6 [hp_X]/59 mL; ARSENIC TRIOXIDE 12 [hp_X]/59 mL; HELICOBACTER PYLORI 30 [hp_X]/59 mL
INACTIVE INGREDIENTS: ALCOHOL; WATER

C94

ACTIVE INGREDIENTS

Glycyrrhiza glabra 2X
Natrum phosphoricum 2X
Oryza sativa 2X
Panicum miliaceum 2X
Plantago lanceolata 2X
Poria 2X
Raphanus sativus 2X
Sinapis nigra 2X
Triticum repens 2X
Zingiber officinale 2X
Hydrastis canadensis 5X
Carbo vegetabilis 6X
Symphytum officinale 6X
Arsenicum album 12X
Helicobacter pylori 30X

QUESTIONS

Professional Formulas

PO Box 2034 Lake Oswego, OR 97035

INDICATIONS

For temporary relief of minor pain in the upper abdomen, heartburn, indigestion, flatulence, or nausea.*

PURPOSE

*Claims based on traditional homeopathic practice, not accepted medical evidence. Not FDA evaluated.

WARNINGS

Severe or persistent symptoms may be a sign of a serious condition. Consult a doctor promptly if symptoms persist or are accompanied by a fever, vomiting, diarrhea, or loss of appetite. Keep out of the reach of children. In case of overdose, get medical help or contact a poison control center right away. If pregnant or breastfeeding, ask a healthcare professional before use.

Keep out of the reach of children.

PREGNANCY OR BREAST FEEDING

If pregnant or breastfeeding, ask a healthcare professional before use.

DIRECTIONS

Place drops under tongue 30 minutes before/after meals. Adults and children 12 years and over: Take 10 drops up to 3 times per day. Consult a physician for use in children under 12 years of age.

OTHER INFORMATION

Tamper resistant. If seal is broken, do not use. After opening, close container tightly and store at room temperature away from heat.

INACTIVE INGREDIENTS

10% ethanol, purified water, 8% vegetable glycerin (from soy).

LABEL

Est 1985

Professional Formulas

Complementary Health

Ulcer Drops

Homeopathic Remedy

2 FL. OZ. (59 mL)